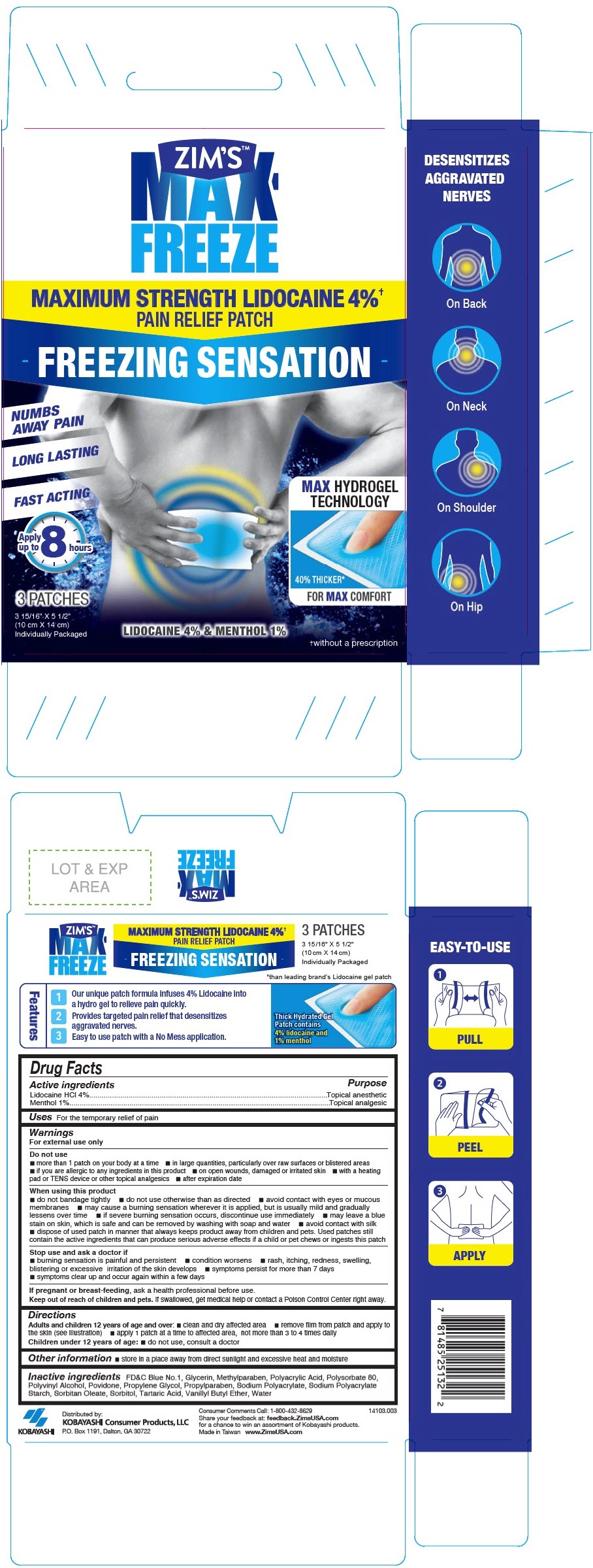 DRUG LABEL: ZIMS MAX FREEZE
NDC: 54273-012 | Form: PATCH
Manufacturer: KOBAYASHI Healthcare International, Inc.
Category: otc | Type: HUMAN OTC DRUG LABEL
Date: 20251218

ACTIVE INGREDIENTS: LIDOCAINE HYDROCHLORIDE 760 mg/1 1; MENTHOL, UNSPECIFIED FORM 190 mg/1 1
INACTIVE INGREDIENTS: SODIUM POLYACRYLATE STARCH (400 MICROMETER PARTICLE); FD&C BLUE NO. 1; GLYCERIN; METHYLPARABEN; POLYACRYLIC ACID (300000 MW); POLYVINYL ALCOHOL, UNSPECIFIED; POVIDONE, UNSPECIFIED; PROPYLENE GLYCOL; PROPYLPARABEN; SODIUM POLYACRYLATE (2500000 MW); SORBITAN MONOOLEATE; SORBITOL; TARTARIC ACID; VANILLYL BUTYL ETHER; WATER; POLYSORBATE 80

ZIM'S™ MAX FREEZE

Drug Facts

ACTIVE INGREDIENT

Active ingredients | Purpose
Lidocaine HCl 4% | Topical anesthetic
Menthol 1% | Topical analgesic

Uses

For the temporary relief of pain

Warnings

For external use only

Do not use

- more than 1 patch on your body at a time
- in large quantities, particularly over raw surfaces or blistered areas
- if you are allergic to any ingredients in this product
- on open wounds, damaged or irritated skin
- with a heating pad or TENS device or other topical analgesics
- after expiration date

When using this product

- do not bandage tightly
- do not use otherwise than as directed
- avoid contact with eyes or mucous membranes
- may cause a burning sensation wherever it is applied, but is usually mild and gradually lessens over time
- if severe burning sensation occurs, discontinue use immediately
- may leave a blue stain on skin, which is safe and can be removed by washing with soap and water
- avoid contact with silk
- dispose of used patch in manner that always keeps product away from children and pets. Used patches still contain the active ingredients that can produce serious adverse effects if a child or pet chews or ingests this patch

Stop use and ask a doctor if

- burning sensation is painful and persistent
- condition worsens
- rash, itching, redness, swelling, blistering or excessive irritation of the skin develops
- symptoms persist for more than 7 days
- symptoms clear up and occur again within a few days

PREGNANCY OR BREAST FEEDING

If pregnant or breast-feeding, ask a health professional before use.

Keep out of reach of children and pets. If swallowed, get medical help or contact a Poison Control Center right away.

Directions

Adults and children 12 years of age and over:

- clean and dry affected area
- remove film from patch and apply to the skin (see illustration)
- apply 1 patch at a time to affected area, not more than 3 to 4 times daily

Children under 12 years of age:

- do not use, consult a doctor

Other information

- store in a place away from direct sunlight and excessive heat and moisture

Inactive ingredients

FD&C Blue No.1, Glycerin, Methylparaben, Polyacrylic Acid, Polysorbate 80, Polyvinyl Alcohol, Povidone, Propylene Glycol, Propylparaben, Sodium Polyacrylate, Sodium Polyacrylate Starch, Sorbitan Oleate, Sorbitol, Tartaric Acid, Vanillyl Butyl Ether, Water

Distributed by:
KOBAYASHI Consumer Products, LLC
P.O. Box 1191, Dalton, GA 30722

PRINCIPAL DISPLAY PANEL - 3 Patch Pouch Box

ZIM'S™
MAX-
FREEZE

MAXIMUM STRENGTH LIDOCAINE 4%†
PAIN RELIEF PATCH

FREEZING SENSATION

NUMBS
AWAY PAIN

LONG LASTING

FAST ACTING

Apply
up to
8 hours

MAX HYDROGEL
TECHNOLOGY

40% THICKER*
FOR MAX COMFORT

3 PATCHES

3 15/16" X 5 1/2"
(10 cm X 14 cm)
Individually Packaged

LIDOCAINE 4% & MENTHOL 1%

†without a prescription